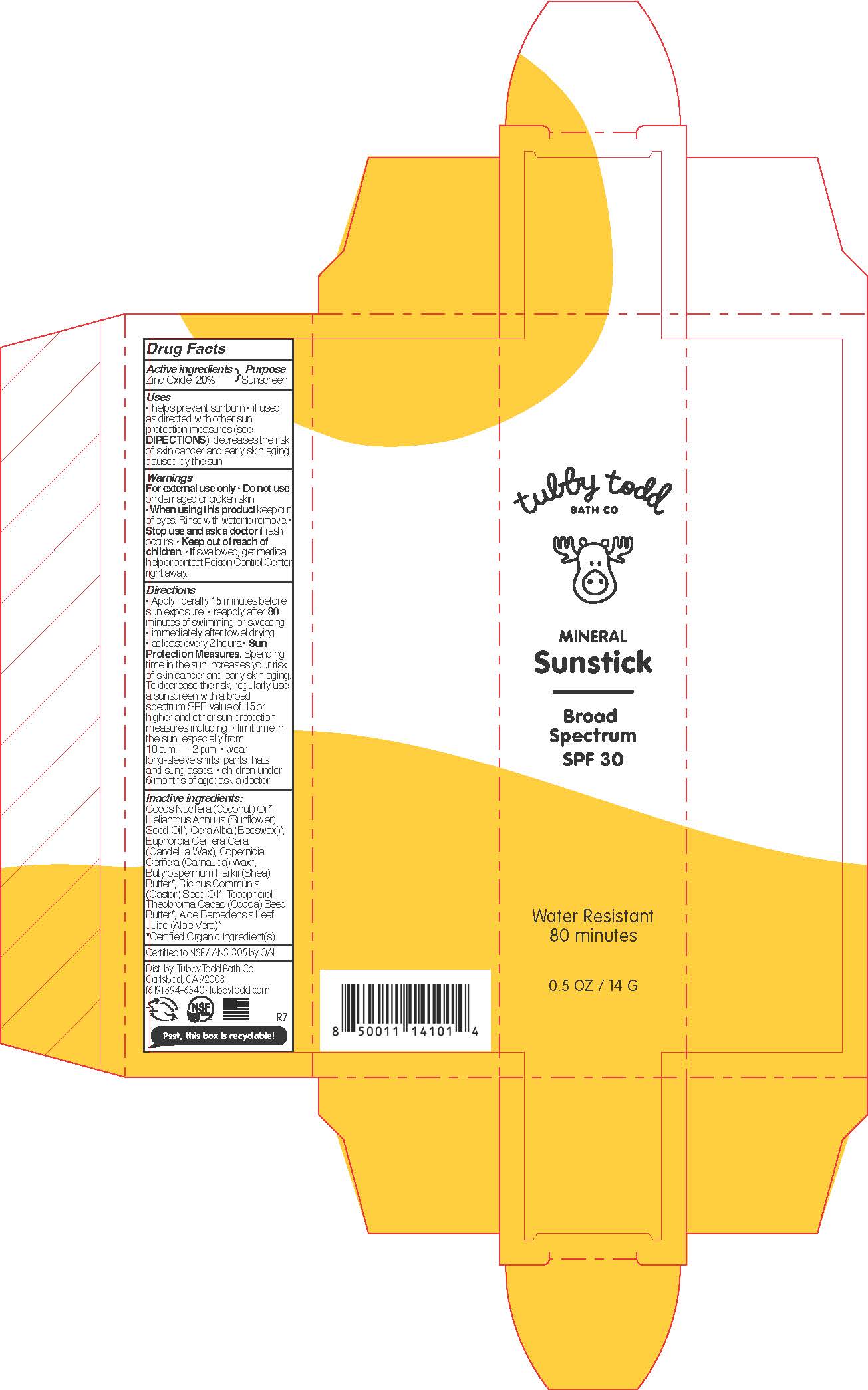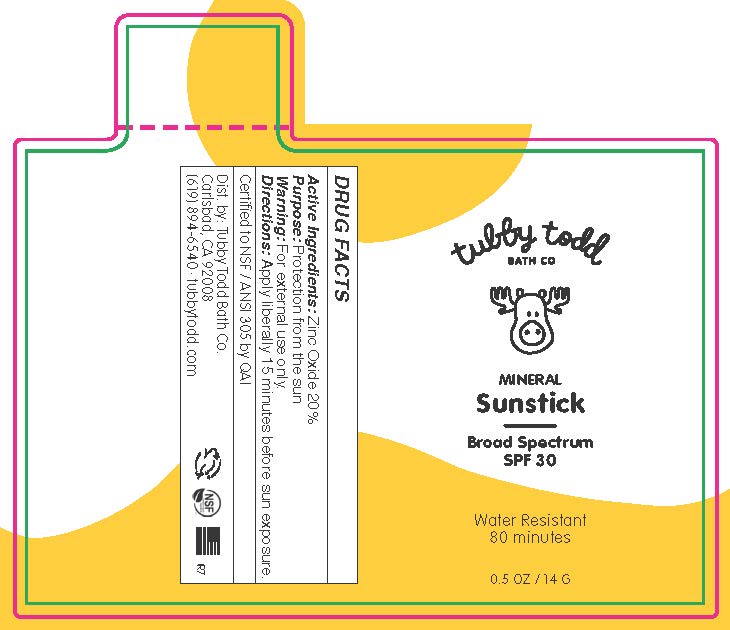 DRUG LABEL: Mineral Sunstick
NDC: 73088-108 | Form: STICK
Manufacturer: Tubby Todd
Category: otc | Type: HUMAN OTC DRUG LABEL
Date: 20241222

ACTIVE INGREDIENTS: ZINC OXIDE 20 g/100 g
INACTIVE INGREDIENTS: BUTYROSPERMUM PARKII (SHEA) BUTTER; HELIANTHUS ANNUUS (SUNFLOWER) SEED OIL; BEESWAX; COCOS NUCIFERA (COCONUT) OIL; THEOBROMA CACAO (COCOA) SEED BUTTER; TOCOPHEROL; RICINUS COMMUNIS (CASTOR) SEED OIL; ALOE BARBADENSIS LEAF JUICE; EUPHORBIA CERIFERA (CANDELILLA) WAX; COPERNICIA CERIFERA (CARNAUBA) WAX

Mineral Sunstick SPF 30

Active ingredients

Zinc Oxide 20%

Purpose

Sunscreen

Uses

• Helps prevent sunburn
• If used as directed with other sun protection measures (see Directions), decreases the risk of skin cancer and early skin aging caused by the sun.

Warnings

• For external use only.

• Do not use

on damage or broken skin.

• When using this product

keep out of eyes. Rinse with water to remove.

• Stop use and ask a doctor

if skin rash occurs.

• Keep out of reach of children.

If swallowed, get medical help or contact Poison Control Center right away.

Directions

• Apply liberally 15 minutes before sun exposure.
• Reapply
-after 80 minutes of swimming or sweating
-immediately after towel drying
-at least every 2 hours
• Sun Protection Measures: Spending time in the sun increases your risk of skin cancer and early skin aging. To decrease the risk, regularly use a sunscreen with a broad spectrum SPF value of 15 or higher and other sun protection measures including:
-limit time in the sun, especially from10am - 2pm
-wear long-sleeve shirts, pants, hats and sunglasses
• Children under 6 months of age: ask a doctor.

Inactive ingredients

Cocos Nucifera (Coconut) Oil*, Helianthus Annuus (Sunflower) Seed Oil*, Cera Alba (Beeswax)*, Euphorbia Cerifera Cera (Candelilla Wax), Copernicia Cerifera (Carnauba) Wax*, Butyrospermum Parkii (Shea) Butter*, Ricinus Communis (Castor) Seed Oil*, Tocopherol Theobroma Cacao (Cocoa) Seed Butter*, Aloe Barbadensis Leaf Juice (Aloe Vera)*
*Certified Organic Ingredient(s)